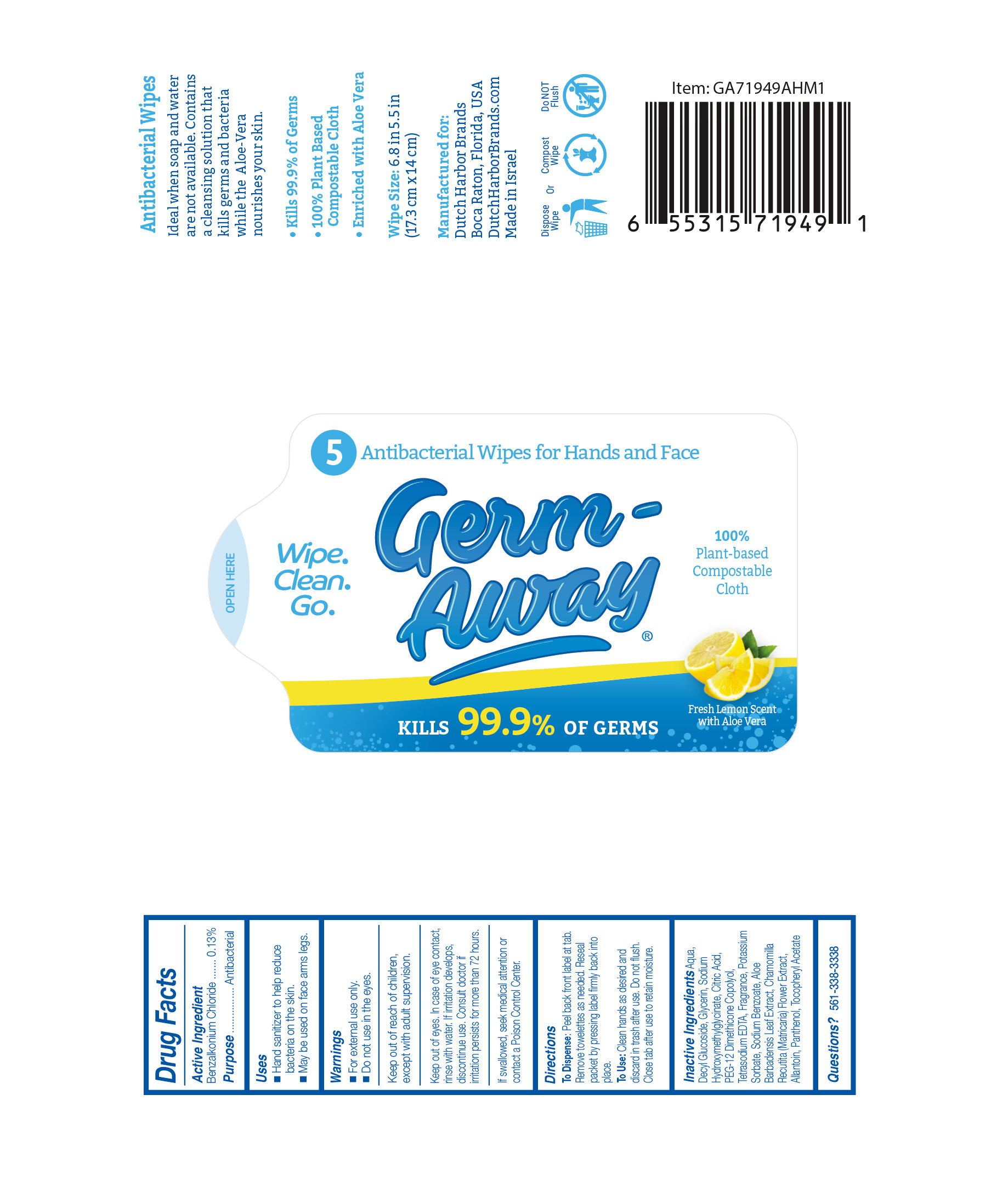 DRUG LABEL: Germ-Away
NDC: 74680-104 | Form: CLOTH
Manufacturer: Unico International Trading Corp
Category: otc | Type: HUMAN OTC DRUG LABEL
Date: 20260108

ACTIVE INGREDIENTS: BENZALKONIUM CHLORIDE 1.3 mg/1 g
INACTIVE INGREDIENTS: DIPHENYL ETHER; EUCALYPTOL; SODIUM BENZOATE; PANTHENOL; PEG-12 DIMETHICONE (300 CST); ALOE VERA LEAF; CP FORMATE; TETRAHYDROLINALOOL; SODIUM HYDROXYMETHYLGLYCINATE; DECYL GLUCOSIDE; POTASSIUM SORBATE; 3,7-DIMETHYL-1-OCTANOL; 2,2'-OXYDIPROPANOL; GLYCERIN; .ALPHA.-TOCOPHEROL ACETATE; EDETATE SODIUM; ALLANTOIN; ANHYDROUS CITRIC ACID; WATER; CHAMOMILE; COUMARIN

Germ-Away

Active Ingredient

Benzalkonium chloride 0.1%

Purpose

Anti-bacterial

Inactive Ingredients

Aqua, Decyl Glucoside, Glycerin, Sodium Hydroxymethylglycinate, Citric Acid, PEG-12 Dimethicone Copolyol, Tetrasodium EDTA, Potassium Sorbate, Sodium Benzoate, Aloe Barbadensis Leaf Extract, Chamomilla Recutita (Matricaria) Flower Extract, Allantoin, Panthenol, Tocopheryl Acetate, Fragrance

Keep out of the reach of children.

Keep out of reach of children, except with adult supervision.

Warnings

For external use only. Do not use in the eyes.

Keep out of eyes. In case of eye contact, rinse with water. If irritation develops, discontinue use. Consult doctor if irritation persists for more than 72 hours.

If swallowed, seek medical attention or contact a Poison Control Center.

Directions

Pull one sheet from pack. Sanitize hands or other affected area. Discard in trash after use. Do not flush. Close tab after use to retain moisture.

To use

Peel back from label at tab. Remove towelettes as needed. Reseal packet by pressing label firmly back into place.